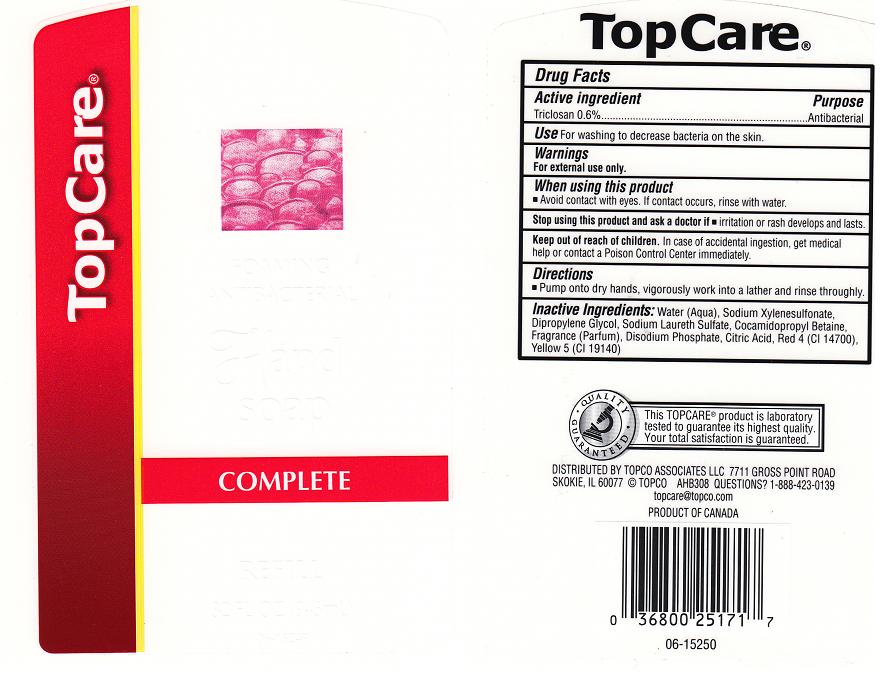 DRUG LABEL: TOPCO
NDC: 36800-178 | Form: LIQUID
Manufacturer: TOPCO ASSOCIATES LLC
Category: otc | Type: HUMAN OTC DRUG LABEL
Date: 20111117

ACTIVE INGREDIENTS: TRICLOSAN 0.6 mL/100 mL
INACTIVE INGREDIENTS: WATER; SODIUM XYLENESULFONATE; DIPROPYLENE GLYCOL; SODIUM LAURETH SULFATE; COCAMIDOPROPYL BETAINE; SODIUM PHOSPHATE; CITRIC ACID MONOHYDRATE; FD&C RED NO. 4; FD&C YELLOW NO. 5

DRUG FACTS

ACTIVE INGREDIENT

TRICLOSAN 0.6%

PURPOSE

ANTIBACTERIAL

USES

FOR WASHING TO DECREASE BACTERIA ON THE SKIN.

WARNINGS

FOR EXTERNAL USE ONLY

WHEN USING THIS PRODUCT

AVOID CONTACT WITH EYES. IF CONTACT OCCURS, RINSE WITH WATER.

STOP USING THIS PRODUCT AND ASK DOCTOR IF

IRRITATION OR RASH DEVELOPS AND LASTS.

KEEP OUT OF REACH OF CHILDREN

IN CASE OF ACCIDENTAL INGESTION, GET MEDICAL HELP OR CONTACT A POISON CONTROL CENTER IMMEDIATELY.

DIRECTIONS

PUMP ONTO DRY HANDS, VIGOROUSLY WORK INTO A RICH LATHER AND RINSE THOROUGHLY.

INACTIVE INGREDIENTS

WATER (AQUA), SODIUM XYLENESULFONATE, DIPROPYLENE GLYCOL, SODIUM LAURETH SULFATE, COCAMIDOPROPYL BETAINE, FRAGRANCE (PARFUM), DISODIUM PHOSPHATE, CITRIC ACID, RED 4 (CI 14700), YELLOW 5 (CI 19140)